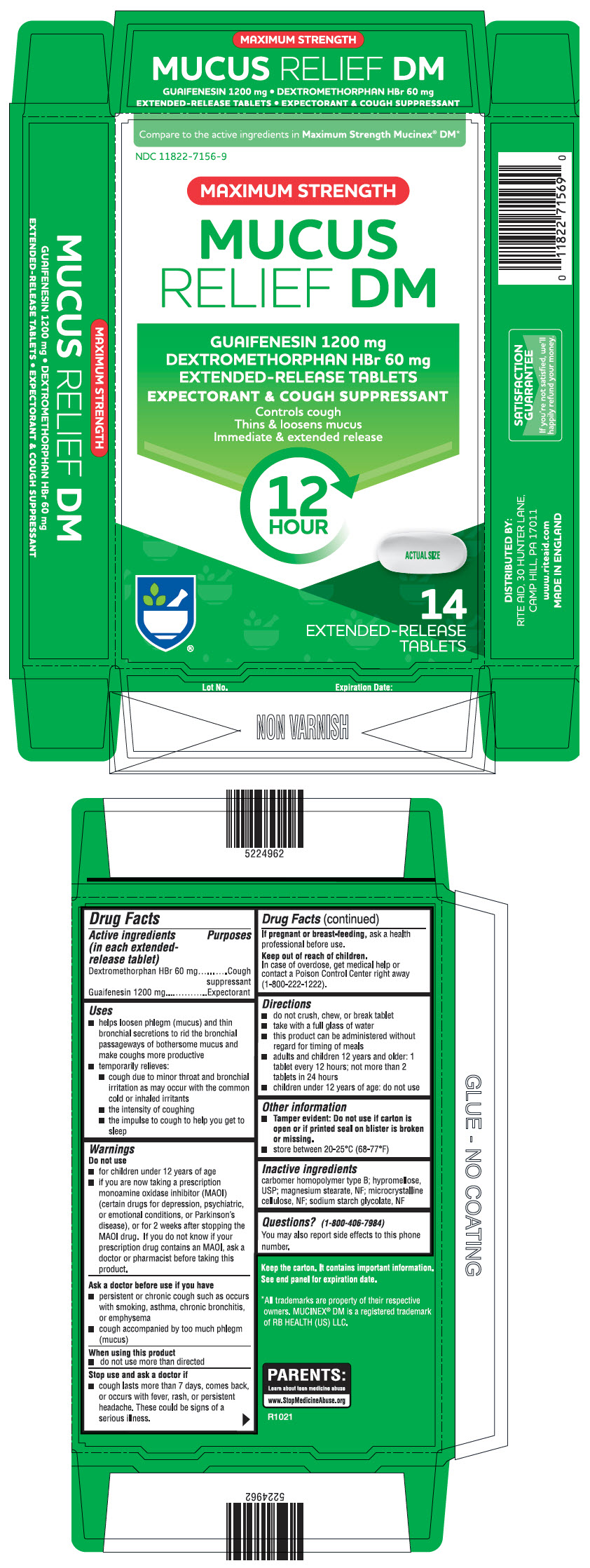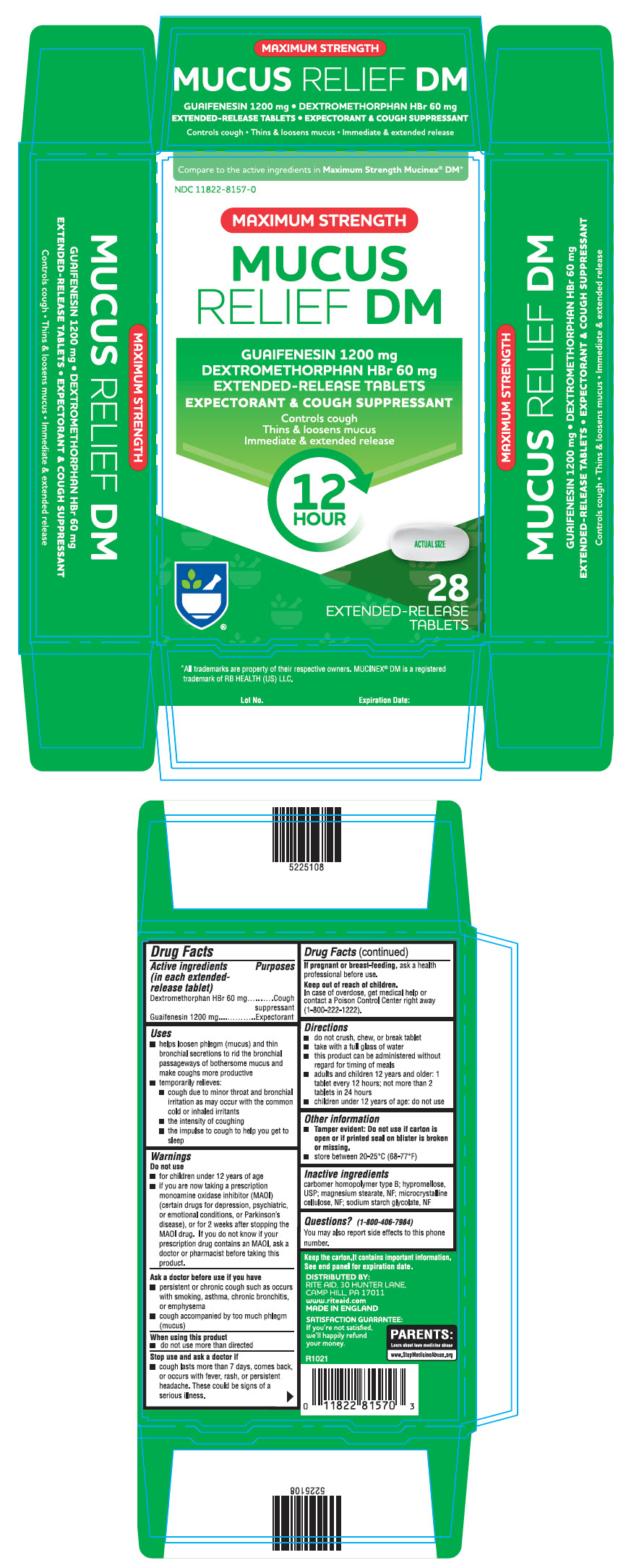 DRUG LABEL: Guaifenesin and Dextromethorphan Hydrobromide
NDC: 11822-7156 | Form: TABLET, EXTENDED RELEASE
Manufacturer: Rite-Aid
Category: otc | Type: HUMAN OTC DRUG LABEL
Date: 20211021

ACTIVE INGREDIENTS: Guaifenesin 1200 mg/1 1; DEXTROMETHORPHAN HYDROBROMIDE 60 mg/1 1
INACTIVE INGREDIENTS: CARBOMER HOMOPOLYMER TYPE B (ALLYL PENTAERYTHRITOL CROSSLINKED); HYPROMELLOSE, UNSPECIFIED; MAGNESIUM STEARATE; MICROCRYSTALLINE CELLULOSE; SODIUM STARCH GLYCOLATE TYPE A POTATO

Guaifenesin and Dextromethorphan Hydrobromide

Drug Facts

ACTIVE INGREDIENT

PURPOSE

Active ingredients (in each extended-release tablet) | Purposes
Dextromethorphan HBr 60 mg | Cough suppressant
Guaifenesin 1200 mg | Expectorant

Uses

- helps loosen phlegm (mucus) and thin bronchial secretions to rid the bronchial passageways of bothersome mucus and make coughs more productive
- temporarily relieves:
  - cough due to minor throat and bronchial irritation as may occur with the common cold or inhaled irritants
  - the intensity of coughing
  - the impulse to cough to help you get to sleep

Warnings

Do not use

- for children under 12 years of age
- if you are now taking a prescription monoamine oxidase inhibitor (MAOI) (certain drugs for depression, psychiatric, or emotional conditions, or Parkinson's disease), or for 2 weeks after stopping the MAOI drug. If you do not know if your prescription drug contains an MAOI, ask a doctor or pharmacist before taking this product.

Ask a doctor before use if you have

- persistent or chronic cough such as occurs with smoking, asthma, chronic bronchitis, or emphysema
- cough accompanied by too much phlegm (mucus)

When using this product

- do not use more than directed

Stop use and ask a doctor if

- cough lasts more than 7 days, comes back, or occurs with fever, rash, or persistent headache. These could be signs of a serious illness.

PREGNANCY OR BREAST FEEDING

If pregnant or breast-feeding, ask a health professional before use.

Keep out of reach of children.

In case of overdose, get medical help or contact a Poison Control Center right away (1-800-222-1222).

Directions

- do not crush, chew, or break tablet
- take with a full glass of water
- this product can be administered without regard for timing of meals
- adults and children 12 years and older: 1 tablet every 12 hours; not more than 2 tablets in 24 hours
- children under 12 years of age: do not use

Other information

- Tamper evident: Do not use if carton is open or if printed seal on blister is broken or missing.
- store between 20-25°C (68-77°F)

Inactive ingredients

carbomer homopolymer type B; hypromellose, USP; magnesium stearate, NF; microcrystalline cellulose, NF; sodium starch glycolate, NF

Questions?

(1-800-406-7984)

You may also report side effects to this phone number.

DISTRIBUTED BY: WALGREEN CO.
200 WILMOT RD., DEERFIELD, IL 60015

PRINCIPAL DISPLAY PANEL - 14 Tablet Blister Pack Carton

Compare to the active ingredients in Maximum Strength Mucinex® DM*

NDC 11822-7156-9

MAXIMUM STRENGTH

MUCUS
RELIEF DM

GUAIFENESIN 1200 mg
DEXTROMETHORPHAN HBr 60 mg
EXTENDED-RELEASE TABLETS
EXPECTORANT & COUGH SUPPRESSANT

Controls cough
Thins & loosens mucus
Immediate & extended release

12
HOUR

ACTUAL SIZE

14
EXTENDED-RELEASE
TABLETS

PRINCIPAL DISPLAY PANEL - 28 Tablet Blister Pack Carton

Compare to the active ingredients in Maximum Strength Mucinex® DM*

NDC 11822-8157-0

MAXIMUM STRENGTH

MUCUS
RELIEF DM

GUAIFENESIN 1200 mg
DEXTROMETHORPHAN HBr 60 mg
EXTENDED-RELEASE TABLETS
EXPECTORANT & COUGH SUPPRESSANT

Controls cough
Thins & loosens mucus
Immediate & extended release

12
HOUR

ACTUAL SIZE

28
EXTENDED-RELEASE
TABLETS